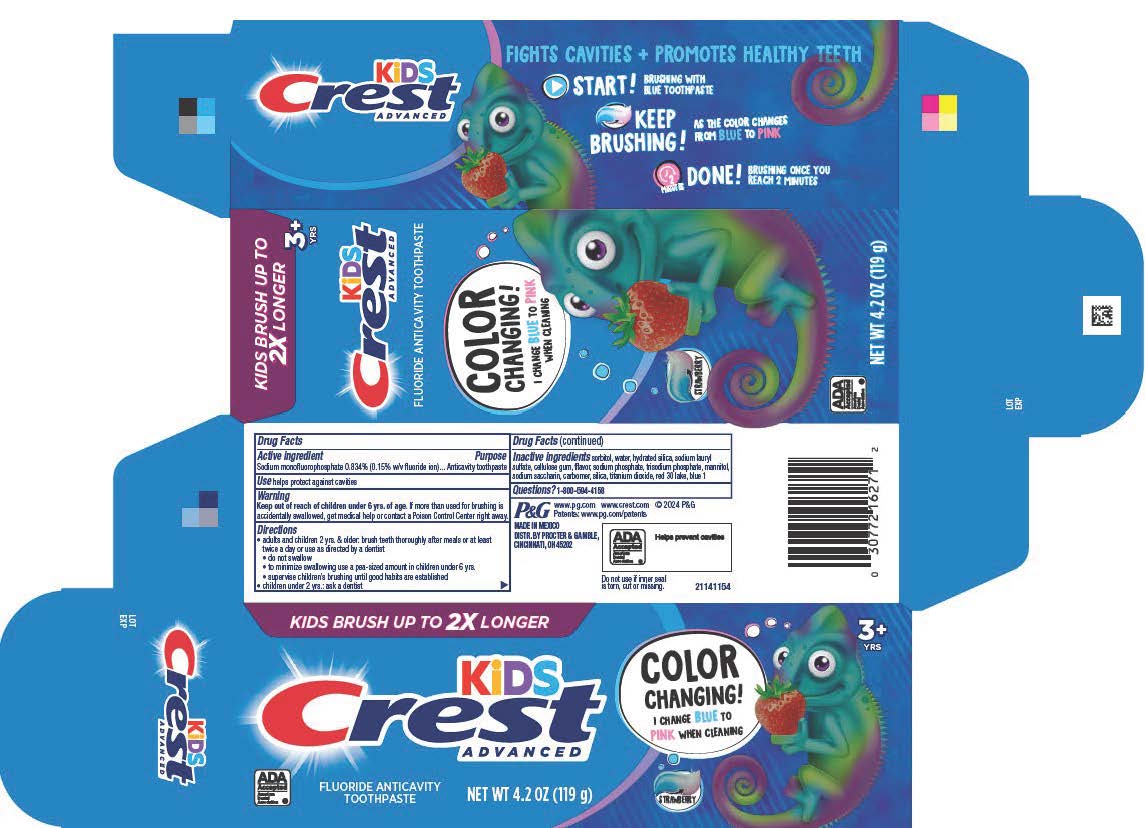 DRUG LABEL: Crest Kids Advanced Color Changing
NDC: 58933-024 | Form: PASTE, DENTIFRICE
Manufacturer: Procter & Gamble Manufactura, S de R.L. de C.V.
Category: otc | Type: HUMAN OTC DRUG LABEL
Date: 20260107

ACTIVE INGREDIENTS: SODIUM MONOFLUOROPHOSPHATE 1.5 mg/1 g
INACTIVE INGREDIENTS: SODIUM SACCHARIN; SODIUM PHOSPHATE; CELLULOSE GUM; SILICA DIMETHYL SILYLATE; WATER; MANNITOL; HYDRATED SILICA; FD&C BLUE NO. 1; SORBITOL; SODIUM PHOSPHATE, TRIBASIC, ANHYDROUS; SODIUM LAURYL SULFATE; D&C RED NO. 30; TITANIUM DIOXIDE; CARBOMER

Crest Kids Advanced Color Changing

Active Ingredient

Sodium monofluorophosphate 0.834% (0.15% w/v fluoride ion)

Purpose

Anticavity toothpaste

Use

helps protect against cavities

Warnings

Keep out of reach of children under 6 yrs. of age. If more than used for brushing is accidentally swallowed, get medical help or contact a Poison Control Center right away.

Keep out of reach of children under 6 yrs. of age. If more than used for brushing is accidentally swallowed, get medical help or contact a Poison Control Center right away.

Directions

• adults and children 2 yrs. of age and older: brush teeth thoroughly after meals or at least twice a day or as directed by a dentist

• do not swallow

• to minimize swallowing use a pea-sized amount in children under 6 yrs.

• supervise children's brushing until good habits are established

• children under 2 yrs.: ask a dentist

Inactive ingredients

sorbitol, water, hydrated silica, sodium lauryl sulfate, cellulose gum, flavor, sodium phosphate, trisodium phosphate, mannitol, sodium saccharin, carbomer, silica, titanium dioxide, red 30 lake, blue 1

Questions?

1-800-594-4158

DISTR. BY PROCTER & GAMBLE

CINCINNATI, OH 45202

PRINCIPAL DISPLAY PANEL - Crest Kids Advanced Color Changing

KIDS BRUSH UP TO 2X LONGER
3+ YRS
KID'S Crest ADVANCED
FLUORIDE ANTICAVITY TOOTHPASTE
COLOR CHANGING
I CHANGE BLUE TO PINK WHEN CLEANING
STRAWBERRY

ADA

American

Dental Association

NET WT 4.2 OZ (119 g)